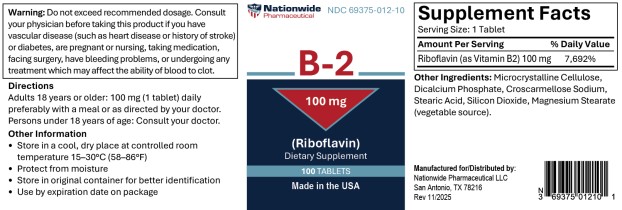 DRUG LABEL: Riboflavin 100mg Tab
NDC: 69375-012 | Form: TABLET
Manufacturer: Nationwide Pharmaceutical LLC
Category: other | Type: DIETARY SUPPLEMENT
Date: 20251205

ACTIVE INGREDIENTS: RIBOFLAVIN 100 mg/1 1

B-2 (RIBOFLAVIN)- Riboflavin tablet
Nationwide Pharmaceutical LLC
----------
B-2 (Riboflavin)

Warning

Do not exceed recommended dosage. Consult your physician before taking this product if you have vascular disease (such as heart disease or history of stroke) or diabetes, are pregnant or nursing, taking medication, facing surgery, have bleeding problems, or undergoing any treatment which may affect the ability of blood to clot.

Directions

Adults 18 years or older: 100 mg (1 tablet) daily preferably with a meal or as directed by your doctor.

Persons under 18 years of age: Consult your doctor.

Other Information

- Store in a cool, dry place at controlled room temperature 15-30°C (58-86°F)
- Protect from moisture
- Store in original container for better identification
- Use by expiration date on package

Supplement Facts

Serving Size: 1 Tablet

Amount Per Tablet

% Daily Value

Riboflavin (as Vitamin B2)

100 mg

7,692%

Other Ingredients: Microcrystalline Cellulose, Dicalcium Phosphate, Croscarmellose Sodium, Stearic Acid, Silicon Dioxide, Magnesium Stearate (vegetable source)

Manufactured for/Distributed by:
Nationwide Pharmaceutical LLC
San Antonio, TX 78216
Rev 11/2025

PRINCIPAL DISPLAY PANEL - 100 mg Tablet Bottle Label

Nationwide
Pharmaceutical
NDC 69375-012-10

B-2

100 mg

(Riboflavin)

Dietary Supplement

100 TABLETS

Made in the USA